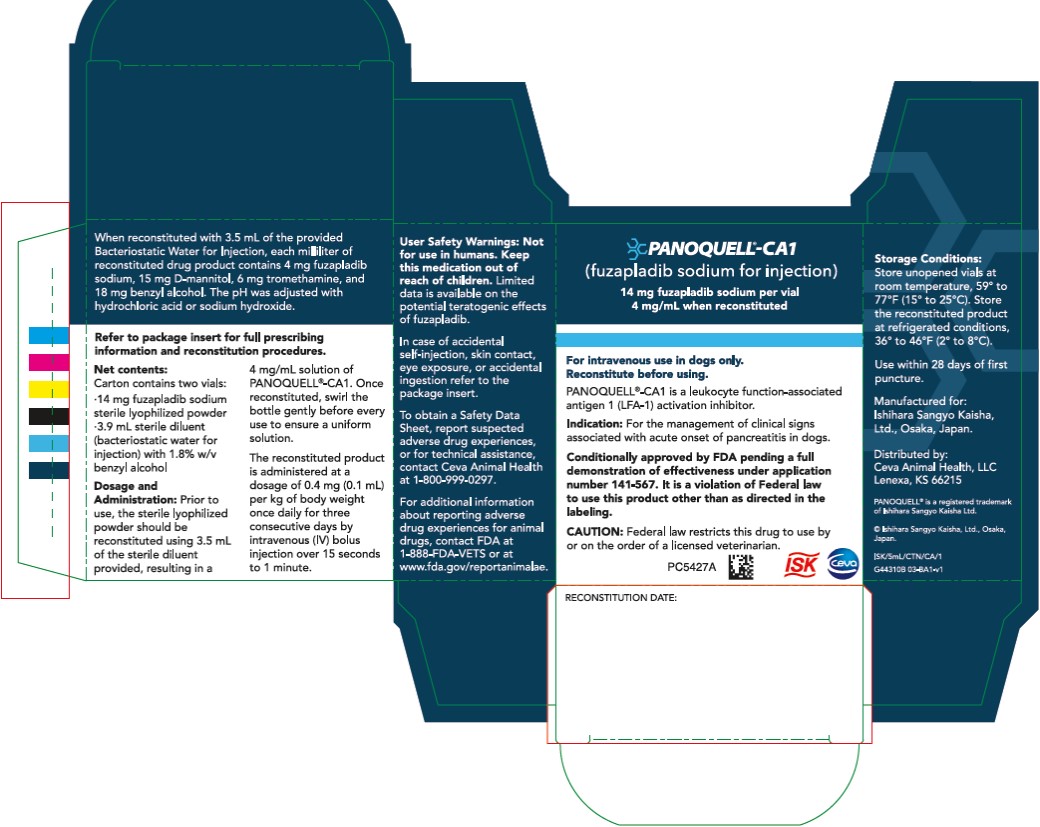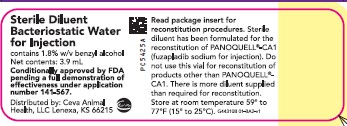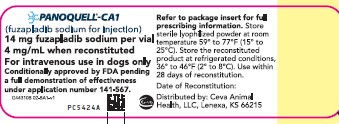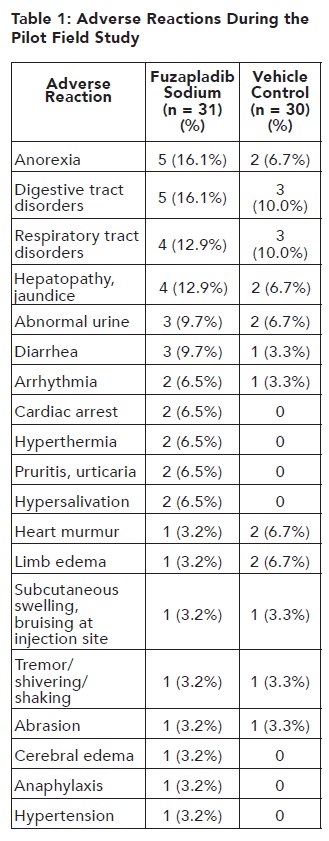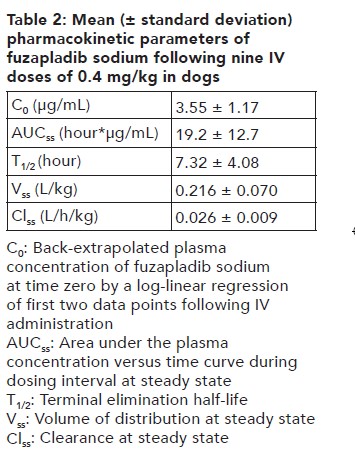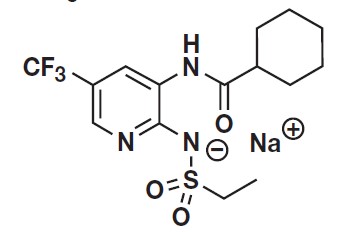 DRUG LABEL: PANOQUELL
NDC: 13744-812 | Form: INJECTION, POWDER, LYOPHILIZED, FOR SOLUTION
Manufacturer: Ceva Sante Animale
Category: animal | Type: PRESCRIPTION ANIMAL DRUG LABEL
Date: 20230322

ACTIVE INGREDIENTS: IS-741 SODIUM 4 mg/1 mL
INACTIVE INGREDIENTS: MANNITOL 15 mg/1 mL; TROMETHAMINE 6 mg/1 mL; BENZYL ALCOHOL 18 mg/1 mL; WATER

PANOQUELL®-CA1

(fuzapladib sodium for injection)

4 mg/mL when reconstituted

Leukocyte function-associated antigen 1 (LFA-1) activation inhibitor

For intravenous use in dogs only

CAUTION:Federal law restricts this drug to use by or on the order of a licensed veterinarian.

Conditionally approved by FDA pending a full demonstration of effectiveness under application number 141-567.

It is a violation of Federal law to use this product other than as directed in the labeling.

DESCRIPTION:

PANOQUELL®-CA1 (fuzapladib sodium for injection) is a selective inhibitor of LFA-1. Fuzapladib sodium is the non-proprietary designation for N-[2-((ethylsulfonyl)amino)-5-(trifluoromethyl)-3-pyridinyl] cyclohexanecarboxamide monosodium. PANOQUELL®-CA1 has a molecular weight of 401.38 and the following structural formula:

PANOQUELL®-CA1 consists of two separate vials. One vial contains 14 mg of fuzapladib sodium, 52.5 mg of D-mannitol, and 21 mg of tromethamine as sterile lyophilized powder. The second vial of 3.9 mL sterile diluent (bacteriostatic water for injection), containing 1.8% w/v benzyl alcohol, is for reconstituting the sterile lyophilized powder prior to use. No other diluent should be used. When reconstituted with 3.5 mL of the provided Bacteriostatic Water for Injection, each milliliter of reconstituted drug product contains 4 mg fuzapladib sodium, 15 mg D-mannitol, 6 mg tromethamine, and 18 mg benzyl alcohol. The pH was adjusted with hydrochloric acid or sodium hydroxide.

INDICATIONS:

PANOQUELL®-CA1 is indicated for the management of clinical signs associated with acute onset of pancreatitis in dogs.

DOSAGE AND ADMINISTRATION:

Prior to use, the sterile lyophilized powder should be reconstituted (see Reconstitution Procedures) using the sterile diluent provided, resulting in a 4 mg/mL solution of PANOQUELL®-CA1. Once reconstituted, swirl the bottle gently before every use to ensure a uniform solution.

The reconstituted product is administered at a dosage of 0.4 mg (0.1 mL) per kg body weight once daily for three consecutive days by intravenous (IV) bolus injection over 15 seconds to 1 minute.

Reconstitution Procedures:
The items needed for reconstitution are:

- Sterile PANOQUELL®-CA1 lyophilized powder
- Sterile diluent
- Sterile 5 mL syringe for transfer of diluent
- Sterile needle

Steps for reconstitution:

1. Using a sterile needle and syringe, withdraw 3.5 mL of the sterile diluent from the vial and slowly transfer the sterile diluent into the vial containing the sterile PANOQUELL®-CA1 lyophilized powder through the stopper. There is more sterile diluent supplied than the 3.5 mL needed for reconstitution.
2. Once the sterile diluent has been added to the powder vial, remove the needle and syringe from the vial. Discard unused sterile diluent, syringe, and needle.
3. Gently swirl the vial until the powder is fully reconstituted into solution, leaving no visible residue or undissolved material.
4. Before each use, gently swirl to ensure a uniform solution.
5. Draw up the appropriate dose using a new sterile needle and syringe.
6. Administer the dose promptly after drawing into the dosing syringe.
7. Store any remaining reconstituted product at refrigerated conditions, 36˚ to 46˚F (2˚ to 8˚C). Reconstituted product remains stable under refrigeration for 28 days.

CONTRAINDICATIONS:

Do not use in dogs with a known hypersensitivity to fuzapladib sodium.

WARNINGS:

User Safety Warnings:

Not for use in humans. Keep this medication out of reach of children.
In case of accidental self-injection:

- Seek medical advice immediately and show the package insert or label to the physician.

In case of accidental skin contact:

- Wash the exposed skin with water for at least 15 minutes.
- If redness and swelling occur, seek medical advice immediately and show the package insert or label to the physician.

In case of accidental eye exposure:

- Wash the eyes with water for at least 15 minutes.
- If wearing contact lenses, rinse the eyes first, then remove contacts and continue to rinse with water.
- If redness and swelling occur, seek medical advice immediately and show the package insert or label to the physician.

In case of accidental ingestion:

- Rinse the mouth out with water.
- Do not induce vomiting unless directed to do so by medical personnel.
- Seek medical advice immediately and show the package insert or label to the physician.

Limited data is available on the potential teratogenic effects of fuzapladib sodium. Therefore, anyone who is pregnant, breast feeding, or planning to become pregnant should avoid direct contact with PANOQUELL®-CA1.

Anyone with known hypersensitivity to fuzapladib sodium or to any of the excipients should avoid contact with PANOQUELL®-CA1.

To obtain a Safety Data Sheet, contact Ceva Animal Health, LLC, at 1-800-999-0297 or www.ceva.com.

PRECAUTIONS:

PANOQUELL®-CA1 is highly protein bound. Use with caution with other medications that are highly protein bound. The concomitant use of PANOQUELL®-CA1 with other protein bound drugs has not been studied in dogs. Commonly used protein bound drugs include non-steroidal anti-inflammatory drugs (NSAIDs), anti-emetics, antibiotics, diuretics, and behavioral medications. Drug compatibility should be monitored in patients requiring adjunctive therapy. Concurrent medications used during the pilot effectiveness study with fuzapladib sodium included, but were not limited to, pain medications (excluding NSAIDs), antiemetics, parasiticides, vaccinations, and medications used to treat well-controlled pre-existing conditions.

The safe use of PANOQUELL®-CA1 has not been evaluated in dogs with cardiac disease, hepatic failure, or renal impairment.

The safe use of PANOQUELL®-CA1 has not been evaluated in dogs that are pregnant, lactating, or intended for breeding.

The safe use of PANOQUELL®-CA1 has not been evaluated in dogs less than 6 months of age.

ADVERSE REACTIONS:

In a well-controlled pilot field study to assess the effectiveness and safety of fuzapladib sodium (not commercial formulation) in client-owned dogs diagnosed with acute onset of pancreatitis (see REASONABLE EXPECTATION OF EFFECTIVENESS), 31 dogs administered fuzapladib sodium and 30 dogs administered vehicle control were evaluated for safety. The vehicle control was excipient sterile lyophilized powder solubilized in 1 mL of Sterile Water for Injection, USP. The adverse reactions observed in the study and the number of dogs experiencing each adverse reaction is summarized in Table 1.

In Table 1, digestive tract disorders included regurgitation (1 fuzapladib, 2 vehicle control), vomiting (1 fuzapladib, 1 vehicle control), flatulence (1 fuzapladib), nausea (1 fuzapladib), and enteritis (1 fuzapladib). Respiratory tract disorders included pneumonia (2 fuzapladib, 1 vehicle control), inspiratory crackles (1 fuzapladib, 2 vehicle control), tachypnea (2 fuzapladib), and dyspnea (1 fuzapladib). Abnormal urine included proteinuria (2 fuzapladib, 2 vehicle control), hematuria (2 vehicle control), and malodorous urine (1 fuzapladib). Some of these dogs were reported with more than one abnormality.

Note: Some dogs experienced an adverse reaction on more than one occasion but are only presented once in the table above for each reported adverse reaction. Five out of the 61 enrolled dogs died during the study: four in the fuzapladib sodium group and one in the vehicle control group. Two additional dogs in the vehicle control group were euthanized shortly after completion of the study. Of the seven dogs that died or were euthanized during or after the study, three deaths could be attributed to complications from severe acute onset of pancreatitis: two in the fuzapladib sodium group and one in the vehicle control group. One dog in the fuzapladib sodium group was suspected to have aspiration pneumonia and died after experiencing cardiac arrest. One dog in the vehicle control group was euthanized because of a poor prognosis. Two deaths could be attributed to causes other than acute onset of pancreatitis: one dog in the fuzapladib sodium group had intestinal lymphoma and one vehicle control group dog had a cranial thromboembolic event and a pheochromocytoma.

Foreign Market Experience
The following adverse events were reported voluntarily during post-approval use of the product in dogs in foreign markets: facial and tongue swelling, collapse, and seizure. These adverse events occurred within 24 hours of administration.

CONTACT INFORMATION:
Contact Ceva Animal Health, LLC, at 1-800-999-0297 or www.ceva.com.

To report suspected adverse drug experiences or for technical assistance, contact Ceva Animal Health, LLC, at 1-800-999-0297.

For additional information about reporting adverse drug experiences for animal drugs, contact FDA at 1-888-FDAVETS or at www.fda.gov/reportanimalae

CLINICAL PHARMACOLOGY:

Mechanism of action

PANOQUELL®-CA1 has anti-inflammatory effects through its ability to inhibit activation of LFA-1, resulting in inhibition of inflammatory cell adhesion and migration into sites of tissue injury and inflammation. These anti-inflammatory properties are thought to limit pancreatic lesion expansion and help prevent complications such as multi-organ failure.

Pharmacokinetics

Following once daily IV administration of PANOQUELL®-CA1 at 0.4 mg/kg, 1.2 mg/kg, and 2 mg/kg for nine consecutive days, minimal accumulation was observed with a mean accumulation ratio of 1.37, 1.36, and 1.35, respectively. The extent of plasma exposure (AUC) was greater than dose-proportional between 0.4 and 2 mg/kg after the first dose and ninth dose.

REASONABLE EXPECTATION OF EFFECTIVENESS:

A reasonable expectation of effectiveness may be demonstrated based on evidence such as, but not limited to, pilot data in the target species or studies from published literature.

PANOQUELL®-CA1 is conditionally approved pending a full demonstration of effectiveness. Additional information for Conditional Approvals can be found at www.fda.gov/animalca

The reasonable expectation of effectiveness for PANOQUELL®-CA1 for the management of clinical signs associated with acute onset of pancreatitis
in dogs was based on a pilot field study.

The effectiveness of fuzapladib sodium (not commercial formulation) was demonstrated in a well-controlled pilot field study. A total of 61 client-owned dogs of various breeds between 1.8 and 15.9 years old were enrolled in the study and 36 dogs were included in the effectiveness analysis. Dogs were diagnosed with acute onset of pancreatitis based on clinical signs, clinical pathology results, and a Day 0 canine pancreatic lipase immunoreactivity (cPLI) concentration of ≥ 400 μg/L. Abdominal imaging consisting of ultrasound and/or radiographs were evaluated to exclude cases of gastrointestinal obstruction/foreign body and abdominal masses. Dogs with severe concurrent life-threatening illness other than acute pancreatitis were also excluded. Of the 25 dogs excluded from the effectiveness analysis, most of these dogs (19) began the study before the cPLI results from Day 0 were finalized and were later excluded because their cPLI results were ≤ 400 μg/L. Six dogs were excluded for other reasons.

Of the 36 dogs included in the effectiveness analysis, 17 dogs received 0.4 mg/kg fuzapladib sodium and 19 dogs received 0.1 mL/kg vehicle control
(excipient lyophilized powder solubilized in 1 mL of Sterile Water for Injection, USP) IV once daily for three days. All dogs enrolled in the study received the standard of care for acute onset of pancreatitis, including fluids, nutritional support, pain medications (excluding NSAIDs), anti-emetics, and medications used to treat well-controlled pre-existing conditions. Some dogs also received parasiticides and vaccinations.

A Modified Canine Activity Index (MCAI) was used to evaluate and score the following seven clinical signs relevant in dogs with acute pancreatitis: Activity, Appetite (voluntary food intake), Vomiting, Cranial abdominal pain, Dehydration, Stool consistency, and Blood in the stool.

The primary effectiveness variable was the change in the group mean total MCAI score from Day 0 (pre-treatment) to Day 3, as assessed by the Investigator. Day 0 mean MCAI scores for the fuzapladib sodium and vehicle control groups were 8.53 and 7.68, respectively. The changes in the mean total MCAI scores from Day 0 to 3 for the fuzapladib sodium and vehicle control groups were -7.7 and -5.7, respectively. Dogs treated with fuzapladib sodium had a statistically significant reduction in MCAI scores compared to control (p = 0.0193).

TARGET ANIMAL SAFETY:
In a 9-day laboratory study, 32 healthy intact Beagle dogs (4 dogs/sex/group) aged 6 to 7 months were administered 0.4 (1X), 1.2 (3X), or 2 (5X) mg/kg PANOQUELL®-CA1 (fuzapladib sodium for injection), or saline control, by IV injection once daily for 9 days. All dogs survived to study termination. The administration of PANOQUELL®-CA1 resulted in hypertension and injection site swelling and bruising in a dose dependent manner with increased frequency in the higher dose groups. Hypertension (systolic blood pressure values of ≥ 160 mmHg) was observed only in dogs administered PANOQUELL®-CA1 and occurred only at the end of the study. Mild thrombocytopenia of 121-169 x 10^3/L (reference range: 171- 361 x 10^3/L) was observed in two 0.4 mg/kg group dogs and one 2 mg/kg group dog on one day each. One dog in the 0.4 mg/kg group also had bruising of the injection site that coincided with the thrombocytopenia. One dog in the 2 mg/kg group had pain associated with the injection on the last day of dosing. Focal subcutaneous hemorrhage of the injection sites was observed on gross necropsy in all groups, including control, but increased in severity in a dose dependent manner. On histopathology, observations of increased incidence and severity of dermal fibroplasia, subcutaneous inflammation, and subcutaneous hemorrhage of the injection sites were found only in dogs administered PANOQUELL®-CA1.

HOW SUPPLIED:

PANOQUELL®-CA1 consists of two separate vials. One vial contains 14 mg of fuzapladib sodium, 52.5 mg of D-mannitol, and 21 mg of tromethamine as sterile lyophilized powder. The second vial of 3.9 mL sterile diluent (bacteriostatic water for injection), containing 1.8% w/v benzyl alcohol, is for reconstituting the sterile lyophilized powder prior to use. No other diluent should be used.

STORAGE, HANDLING, AND DISPOSAL:

Store unopened vials at room temperature, 59° to 77°F (15° to 25°C). Store the reconstituted product at refrigerated conditions, 36° to 46°F (2° to 8°C). Use within 28 days of first puncture.

MANUFACTURED FOR:
Ishihara Sangyo Kaisha, Ltd., Osaka, Japan

DISTRIBUTED BY:
Ceva Animal Health, LLC
Lenexa, KS 66215

PANOQUELL® is a registered trademark
of Ishihara Sangyo Kaisha Ltd.

ISK/PAN/P/1
Revision date: 11/22
G44310B 08-BA1-v1

Principal Display Panel - Product Vial

PANOQUELL®-CA1

(fuzapladib sodium for injection)

14 mg fuzapladib sodium per vial

4 mg/mL when reconstituted

For intravenous use in dogs only

Conditionally approved by FDA pending a full demonstration of effectiveness under application number 141-567.

Refer to package insert for full prescribing information. Store unopened vials at room temperature 59° to 77°F (15° to 25°C). Store the reconstituted product at refrigerated conditions, 36° to 46°F (2° to 8°C). Use within 28 days of reconstitution.

Date of reconstitution:

Distributed by: Ceva Animal Health, LLC, Lenexa, KS 66215

Principal Display Panel - Diluent Vial

Sterile Diluent

Bacteriostatic Water for Injection

contains 1.8% w/v benzyl alcohol

Net contents: 3.9 mL

Conditionally approved by FDA pending a full demonstration of effectiveness under application number 141-567.

Distributed by: Ceva Animal Health, LLC, Lenexa, KS 66215

Refer to package insert for reconstitution procedures. Sterile diluent has been formulated for the reconstitution of PANOQUELL®-CA1 (fuzapladib sodium for injection). Do not use this vial for reconstitution of products other than PANOQUELL®-CA1. There is more diluent supplied than required for reconstitution.

Store at room temperature 59° to 77°F (15° to 25°C).

Principal Display Panel - Carton

PANOQUELL®-CA1

(fuzapladib sodium for injection)

14 mg fuzapladib sodium per vial

4 mg/mL when reconstituted

For intravenous use in dogs only.

Reconstitute before using.

PANOQUELL®-CA1 is a leukocyte function-associated antigen 1 (LFA-1) activation inhibitor.

Indication: For the management of clinical signs associated with acute onset of pancreatitis in dogs.

Conditionally approved by FDA pending a full demonstration of effectiveness under application number 141-567. It is a violation of Federal law to use this product other than as directed in the labeling.

CAUTION: Federal law restricts this drug to use by or on the order of a licensed veterinarian.